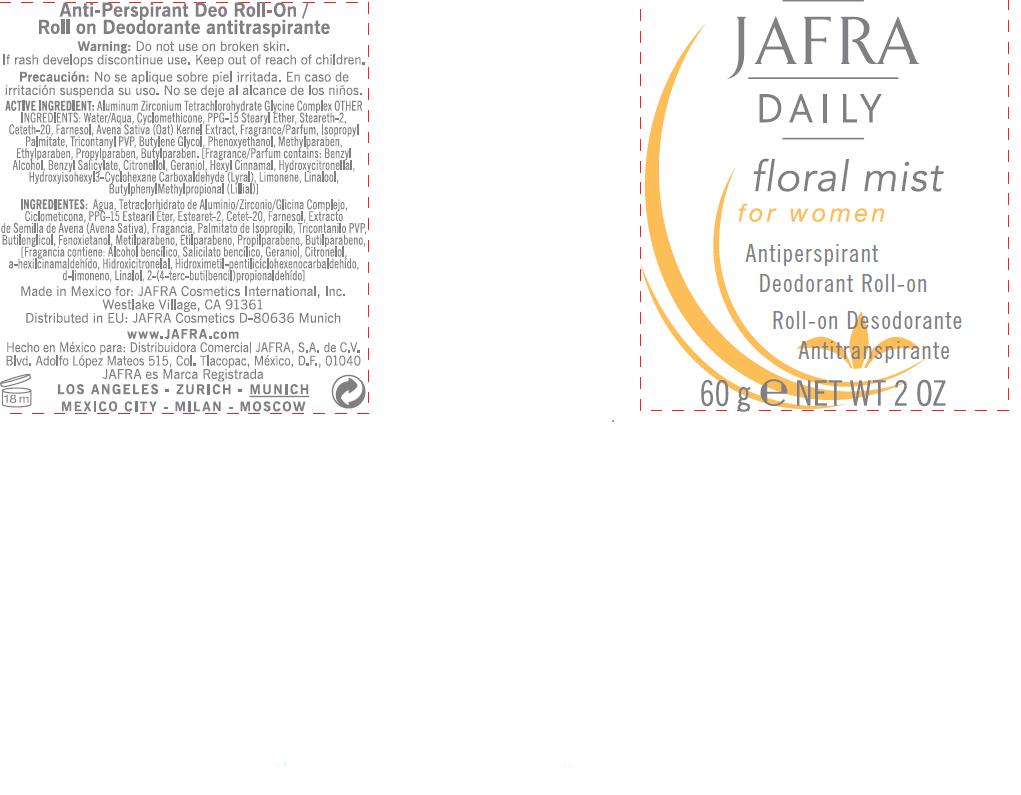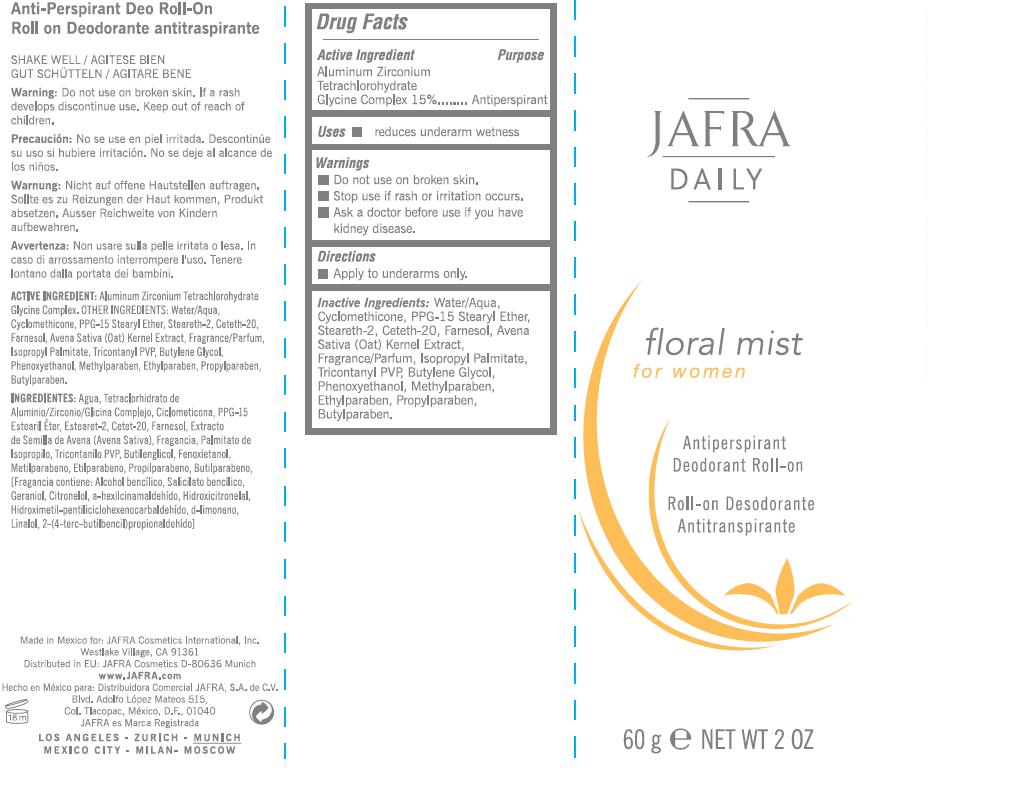 DRUG LABEL: JAFRA DAILY
NDC: 68828-052 | Form: LOTION
Manufacturer: JAFRA COSMETICS INTERNATIONAL
Category: otc | Type: HUMAN OTC DRUG LABEL
Date: 20120501

ACTIVE INGREDIENTS: ALUMINUM ZIRCONIUM TETRACHLOROHYDREX GLY 15 g/100 g
INACTIVE INGREDIENTS: WATER; CYCLOMETHICONE; PPG-15 STEARYL ETHER; STEARETH-2; SORBITAN SESQUIOLEATE; CETETH-20; FARNESOL; OAT; ISOPROPYL PALMITATE; POVIDONE K30; BUTYLENE GLYCOL; PHENOXYETHANOL; METHYLPARABEN; ETHYLPARABEN; PROPYLPARABEN; BUTYLPARABEN

JAFRA DAILY FLORAL MIST

ACTIVE INGREDIENT
ALUMINUM ZIRCONIUM
TETRACHLOROHYDRATE
GLYCINE COMPLEX 15%

PURPOSE

ANTIPERSPIRANT

INACTIVE INGREDIENT

INACTIVE INGREDIENTS: WATER/AQUA, CYCLOMETHICONE, PPG-15 STEARYL ETHER, STEARETH-2, CETETH-20, FARNESOL, AVENA SATIVA (OAT) KERNEL EXTRACT, FRAGRANCE/PARFUM, ISOPROPYL PALMITATE, TRICONTANYL PVP, BUTYLENE GLYCOL, PHENOXYETHANOL, METHYLPARABEN, ETHYLPARABEN, PROPYLPARABEN, BUTYLPARABEN.

USES

- REDUCES UNDERARM WETNESS

DIRECTIONS

- APPLY TO UNDERARMS ONLY

WARNINGS

- DO NOT USE ON BROKEN SKIN.

- STOP USE IF RASH OR IRRITATION OCCURS.

KEEP OUT OF REACH OF CHILDREN.

PACKAGE LABEL

JAFRA

DAILY
FLORAL MIST
FOR WOMEN
ANTIPERSPIRANT
DEODORANT ROLL-ON
60 G / NET WT 2 OZ

- ASK A DOCTOR BEFORE USE IF YOU HAVE KIDNEY DISEASE.